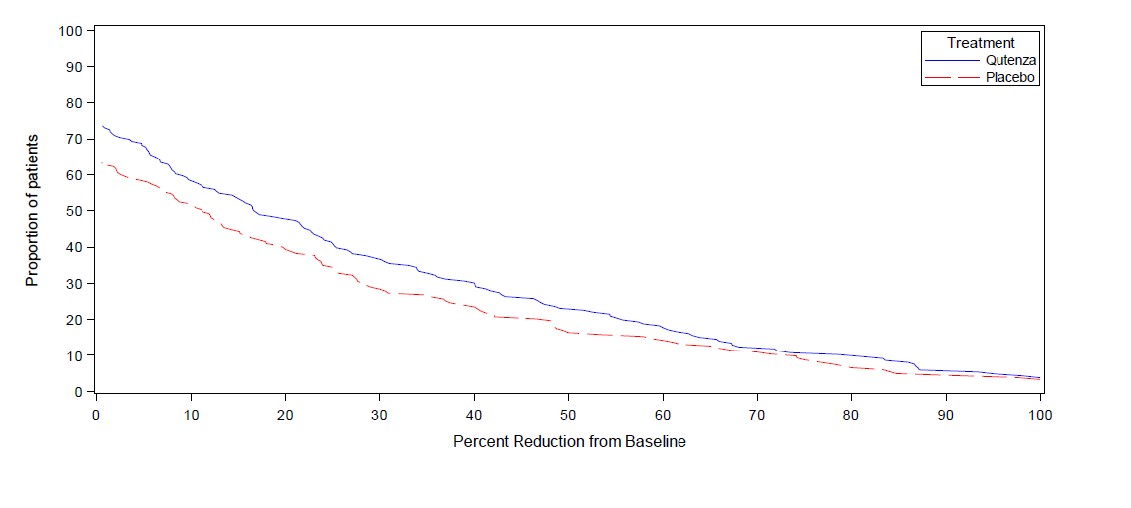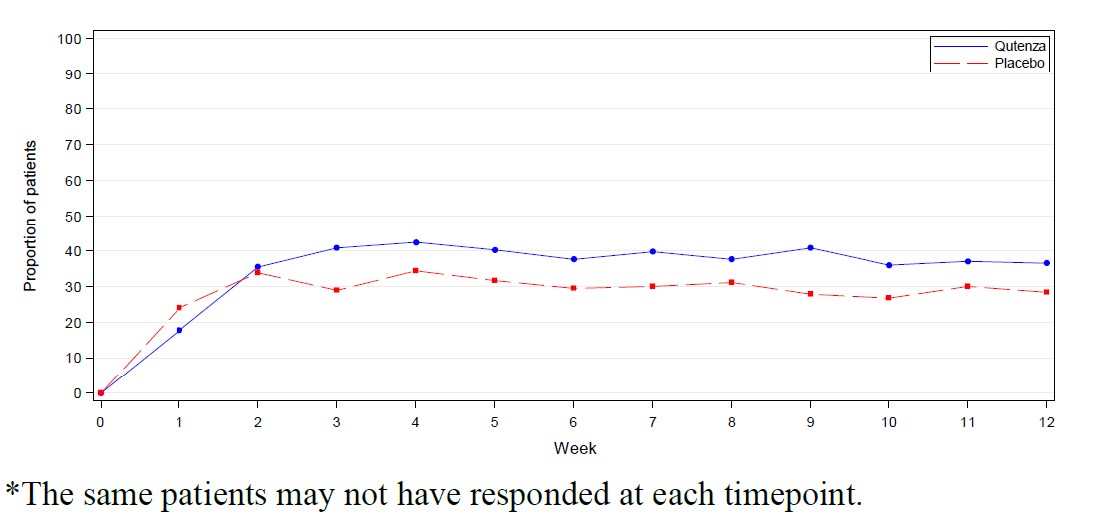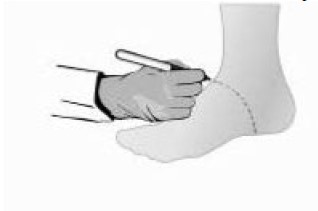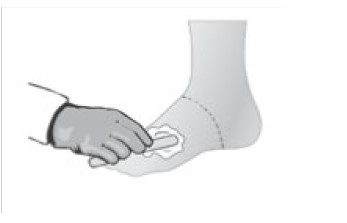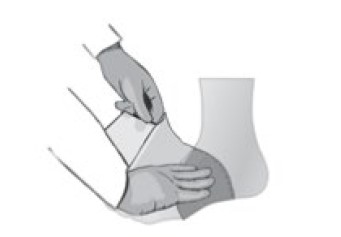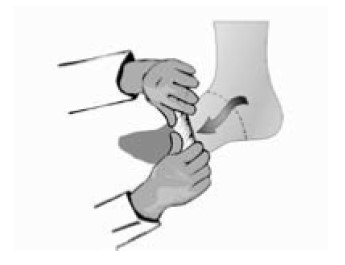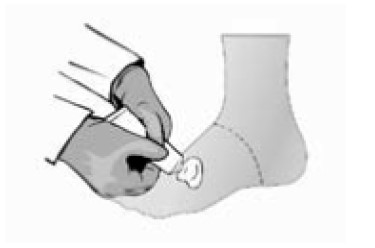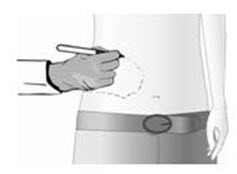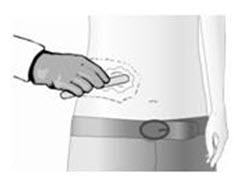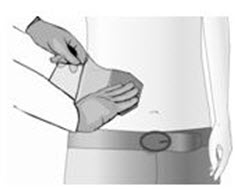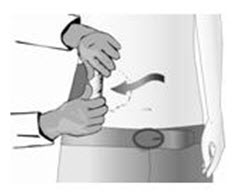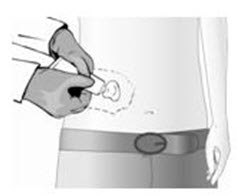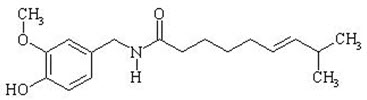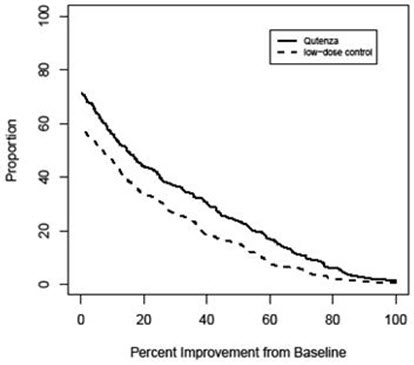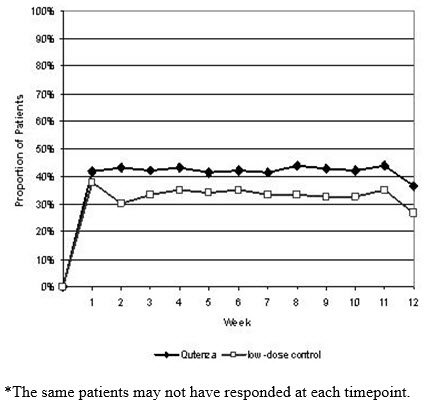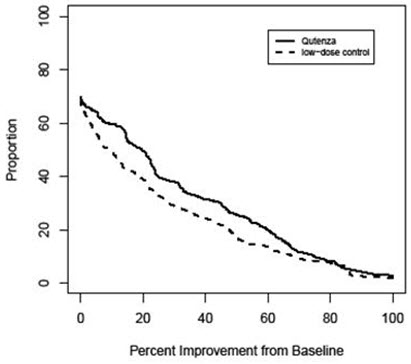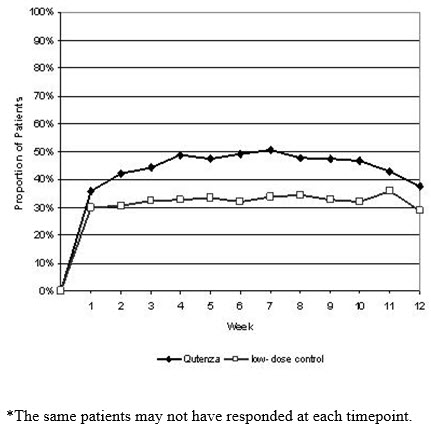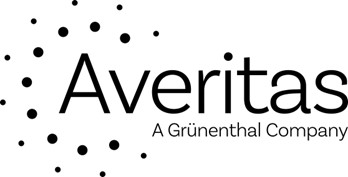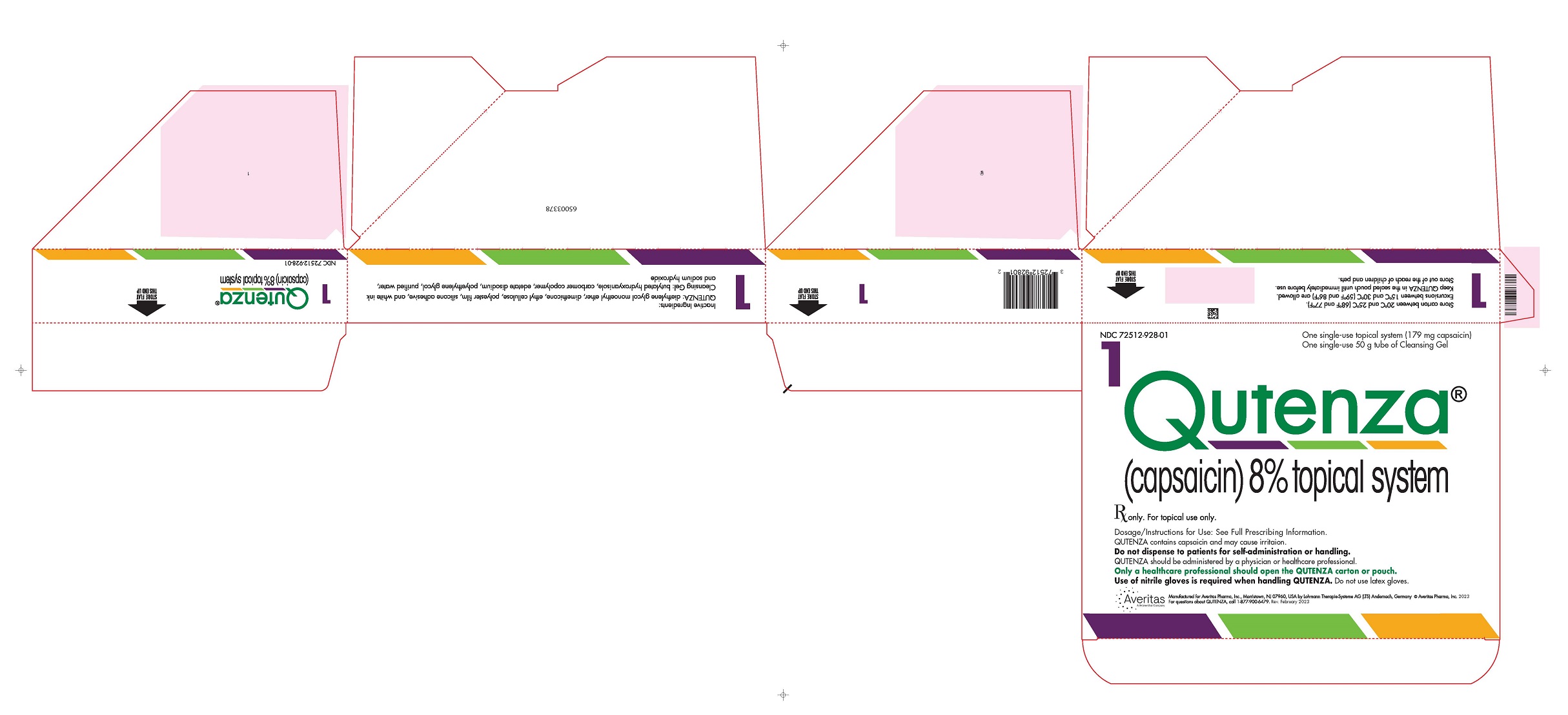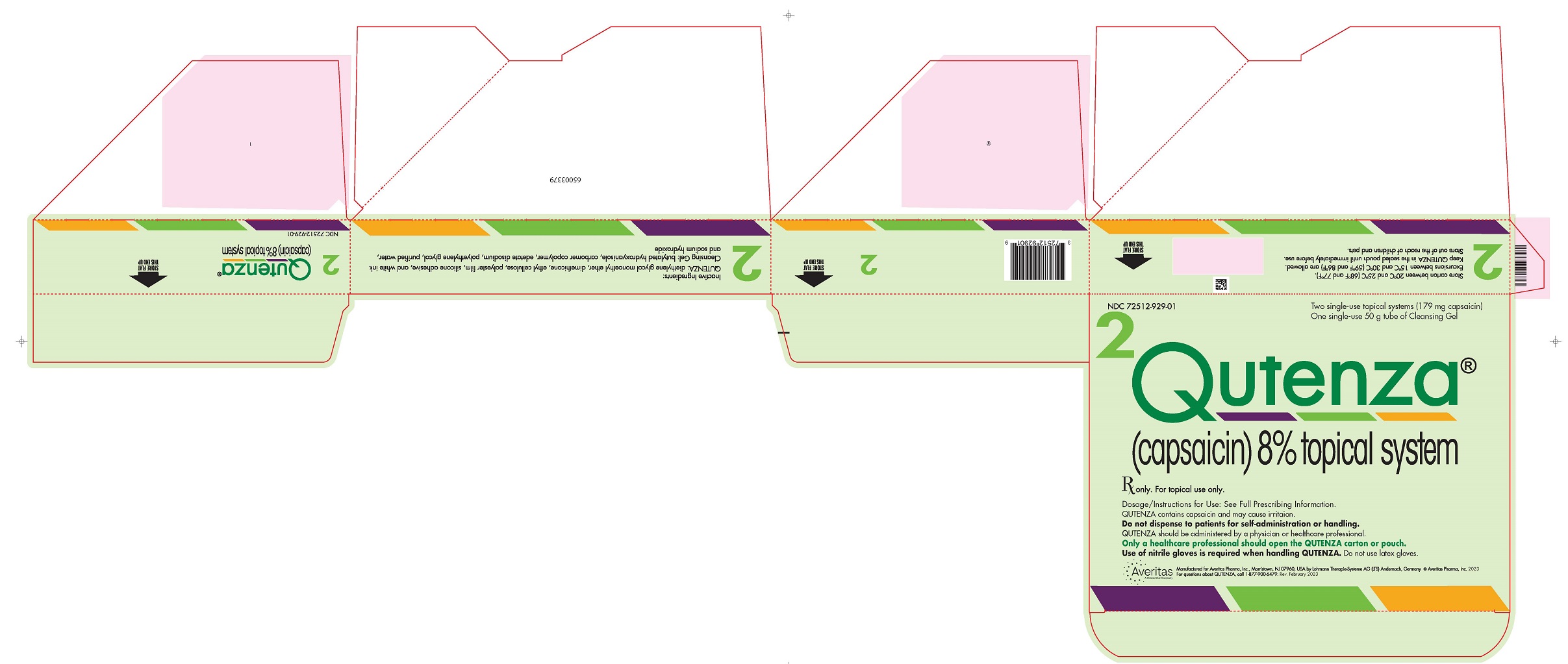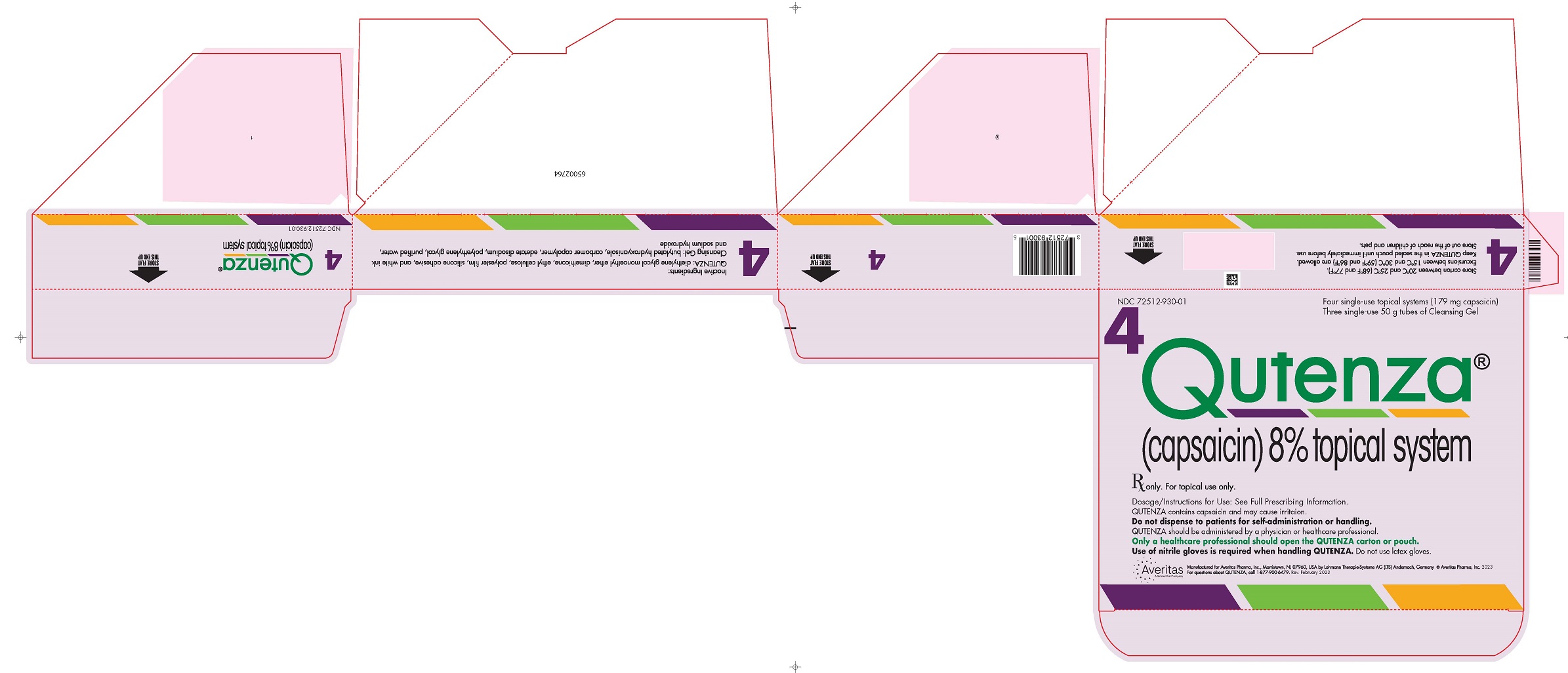 DRUG LABEL: Qutenza
NDC: 72512-928 | Form: KIT | Route: CUTANEOUS
Manufacturer: Averitas Pharma Inc
Category: prescription | Type: HUMAN PRESCRIPTION DRUG LABEL
Date: 20240708

ACTIVE INGREDIENTS: CAPSAICIN 179 mg/179 mg
INACTIVE INGREDIENTS: DIETHYLENE GLYCOL MONOETHYL ETHER; DIMETHICONE; ETHYLCELLULOSE, UNSPECIFIED

HIGHLIGHTS OF PRESCRIBING INFORMATION

These highlights do not include all the information needed to use QUTENZA safely and effectively. See full prescribing information for QUTENZA.
QUTENZA® (capsaicin) topical system
Initial U.S. Approval: 2009

RECENT MAJOR CHANGES

Warnings and Precautions (5.2, 5.5) | 07/2024

1 INDICATIONS AND USAGE

QUTENZA is a TRPV1 channel agonist indicated for the treatment of neuropathic pain associated with postherpetic neuralgia (PHN) and neuropathic pain associated with diabetic peripheral neuropathy (DPN) of the feet. (1)

2 DOSAGE AND ADMINISTRATION

- Only physicians or health care professionals are to administer QUTENZA. (2.1)
- Administer QUTENZA in a well-ventilated treatment area. (2.1)
- Wear nitrile (not latex) gloves when handling QUTENZA and when cleaning treatment areas. (2.1)
- Use of a face mask and protective glasses is advisable for healthcare professionals. (2.1)
- Do not use QUTENZA on broken skin. (2.1)
- PHN: Apply up to four topical systems for 60 minutes. (2.2)
- DPN: Apply up to four topical systems for 30 minutes on the feet. (2.2)
- Repeat every 3 months or as warranted by the return of pain (not more frequently than every three months). (2.2)
- See Dosage and Administration, Instructions for Use, for detailed instructions on QUTENZA administration. (2.3)

3 DOSAGE FORMS AND STRENGTHS

- QUTENZA contains 8% capsaicin (640 mcg per cm ^2). Each topical systems contains a total of 179 mg of capsaicin. (3)

4 CONTRAINDICATIONS

- None

5 WARNINGS AND PRECAUTIONS

Severe Irritation with Unintended Capsaicin Exposure: Capsaicin can cause severe irritation of eyes, mucous membranes, respiratory tract, and skin to the healthcare professional, patients, and others. (See Full Prescribing Information for detailed instructions on how to manage this risk. (2.1, 5.1)

Application-Associated Pain: Patients may experience substantial procedural pain and burning upon application of QUTENZA and following removal of QUTENZA. Prepare to treat acute pain during and following the application procedure with local cooling and/or appropriate analgesic medication. (5.2)

Increase in Blood Pressure: Transient increases in blood pressure may occur with QUTENZA treatment. Monitor blood pressure during and following the treatment procedure. (5.3)

Sensory Function: Reductions in sensory function, which were generally minor and temporary, have been reported following administration of QUTENZA. Assess for signs of sensory deterioration or loss prior to each application of QUTENZA. If sensory loss occurs, treatment should be reconsidered. (5.4)

Severe Application Site Burns: Full-thickness (third-degree) and deep partial-thickness (second-degree) burns have been reported following administration of QUTENZA. Ensure that dosage and administration recommendations are followed. (5.5)

6 ADVERSE REACTIONS

The most common adverse reactions (≥5% and greater than control) in all controlled clinical trials are application site erythema, application site pain, and application site pruritus. (6.1)

To report SUSPECTED ADVERSE REACTIONS, contact Averitas Pharma at 1-877-900-6479 or FDA at 1-800-FDA-1088 or www.fda.gov/medwatch.

FULL PRESCRIBING INFORMATION

1 INDICATIONS AND USAGE

QUTENZA is indicated in adults for the treatment of neuropathic pain associated with postherpetic neuralgia (PHN) and for neuropathic pain associated with diabetic peripheral neuropathy (DPN) of the feet.

2 DOSAGE AND ADMINISTRATION

2.1 Important Dosage and Administration Instructions

- Do not dispense QUTENZA to patients for self-administration or handling. Only physicians or healthcare professionals are to administer and handle QUTENZA.
- Unintended exposure to capsaicin can cause severe irritation of eyes, mucous membranes, respiratory tract, and skin in healthcare professionals, patients and others [see Warnings and Precautions (5.1)] .
- Because unintended exposure to capsaicin can cause severe irritation of eyes, mucous membranes, respiratory tract, and skin, when administering QUTENZA, it is important to follow these procedures:

− Administer QUTENZA in a well-ventilated treatment area.
− Wear only nitrile gloves when handling QUTENZA or any item that makes contact with QUTENZA, and when cleaning capsaicin residue from the skin. Do not use latex gloves as they do not provide adequate protection.
− Use of a face mask and protective glasses is advisable for healthcare professionals.
− Keep QUTENZA in the sealed pouch until immediately before use.
− Use QUTENZA only on dry, intact (unbroken) skin.
− In patients treated for neuropathic pain associated with diabetic peripheral neuropathy, a careful examination of the feet should be undertaken prior to each application of QUTENZA to detect skin lesions related to underlying neuropathy or vascular insufficiency. [see Warnings and Precautions (5.4)] .
− During administration, avoid unnecessary contact with any items in the room, including items that the patient may later have contact with, such as horizontal surfaces and bedsheets.
− Aerosolization of capsaicin can occur upon rapid removal of QUTENZA. Therefore, remove QUTENZA gently and slowly by rolling the adhesive side inward [see Warnings and Precautions (5.1)] .
− Immediately after use, clean all areas that had contact with QUTENZA and properly dispose of QUTENZA, associated packaging, Cleansing Gel, gloves, and other treatment materials in accordance with local biomedical waste procedures.
− If QUTENZA is cut, ensure unused pieces are properly disposed of.

2.2 Dosing

- The recommended dose of QUTENZA for neuropathic pain associated with postherpetic neuralgia is a single, 60-minute application of up to four topical systems.
- The recommended dose of QUTENZA for neuropathic pain associated with diabetic peripheral neuropathy is a single, 30-minute application on the feet of up to four topical systems.

Treatment with QUTENZA may be repeated every three months or as warranted by the return of pain (not more frequently than every three months).

2.3 Instructions for Use

USE IN NEUROPATHIC PAIN ASSOCIATED WITH POSTHERPETIC NEURALGIA

(60-MINUTE APPLICATION TIME)

Prepare

- Administer QUTENZA in a well-ventilated treatment area.
- Put on nitrile (not latex) gloves. Use of a face mask and protective glasses is advisable for healthcare professionals.
- Inspect the pouch. Do not use if the pouch has been torn or damaged.

Identify

- The treatment area (painful area including areas of hypersensitivity and allodynia) must be identified by a physician or healthcare professional and marked on the skin.

- If necessary, clip hair (do not shave) in and around the identified treatment area to promote QUTENZA adherence.
- QUTENZA can be cut to match the size and shape of the treatment area. Gently wash the treatment area with mild soap and water, and dry thoroughly.

Anesthetize (optional)

- The treatment area may be pretreated with a topical anesthetic to potentially reduce discomfort associated with the application of QUTENZA.
- Apply topical anesthetic to the entire treatment area and surrounding 1 to 2 cm, and keep the local anesthetic in place until the skin is anesthetized prior to the application of QUTENZA.

- Remove the topical anesthetic with a dry wipe. Gently wash the treatment area with mild soap and water, and dry thoroughly.

Apply

- Tear open the pouch along the three dashed lines and remove QUTENZA.
- Inspect QUTENZA and identify the outer surface backing layer with the printing on one side and the capsaicin-containing adhesive on the other side. The adhesive side of QUTENZA is covered by a clear, unprinted, diagonally cut release liner.
- Cut QUTENZA before removing the protective release liner. Ensure that unused pieces do not make contact with other objects and are disposed of appropriately.
- The diagonal cut in the release liner is to aid in its removal. Peel a small section of the release liner back and place the adhesive side of QUTENZA on the treatment area.
- While you slowly peel back the release liner from under the QUTENZA with one hand, use your other hand to smooth QUTENZA down onto the skin.

- Once QUTENZA is applied, leave in place for 60 minutes (PHN).
- To ensure QUTENZA maintains contact with the treatment area, a dressing, such as rolled gauze, may be used. Remove the nitrile gloves after the application.
- Instruct the patient not to touch QUTENZA or the treatment area.

Remove

- Put on nitrile (not latex) gloves. Remove QUTENZA by gently and slowly rolling inward.

Cleanse

- After removal of QUTENZA, generously apply Cleansing Gel to the treatment area and leave on for at least one minute. Remove Cleansing Gel with a dry wipe and gently wash the area with mild soap and water. Dry thoroughly.

- Dispose of all treatment materials as described [see Dosage and Administration (2.1)] .
- Inform the patient that the treated area may be sensitive for a few days to heat (e.g., hot showers/baths, direct sunlight, vigorous exercise).

USE IN NEUROPATHIC PAIN ASSOCIATED WITH DIABETIC PERIPHERAL NEUROPATHY

(30-MINUTE APPLICATION TIME ON THE FEET)

Prepare

- Administer QUTENZA in a well-ventilated treatment area.
- Put on nitrile (not latex) gloves. Use of a face mask and protective glasses is advisable for healthcare professionals.
- Inspect the pouch. Do not use if the pouch has been torn or damaged.

Identify

- The treatment area (painful area including areas of hypersensitivity and allodynia) must be identified by a physician or healthcare professional and marked on the skin.
- Examine the feet prior to application of QUTENZA to detect skin lesions related to underlying neuropathy or vascular insufficiency.

- If necessary, clip hair (do not shave) in and around the identified treatment area to promote QUTENZA adherence.
- QUTENZA can be cut to match the size and shape of the treatment area. Gently wash the treatment area with mild soap and water, and dry thoroughly.

Anesthetize (optional)

- The treatment area may be pretreated with a topical anesthetic to potentially reduce discomfort associated with the application of QUTENZA.
- Apply topical anesthetic to the entire treatment area and surrounding 1 to 2 cm, and keep the local anesthetic in place until the skin is anesthetized prior to the application of QUTENZA.

- Remove the topical anesthetic with a dry wipe. Gently wash the treatment area with mild soap and water, and dry thoroughly.

Apply

- Tear open the pouch along the three dashed lines and remove QUTENZA.
- Inspect QUTENZA and identify the outer surface backing layer with the printing on one side and the capsaicin-containing adhesive on the other side. The adhesive side of QUTENZA is covered by a clear, unprinted, diagonally cut release liner.
- Cut QUTENZA before removing the protective release liner. Ensure that unused pieces do not make contact with other objects and are disposed of appropriately.
- The diagonal cut in the release liner is to aid in its removal. Peel a small section of the release liner back and place the adhesive side of QUTENZA on the treatment area.
- While you slowly peel back the release liner from under the QUTENZA with one hand, use your other hand to smooth QUTENZA down onto the skin.
- QUTENZA can be wrapped around the dorsal, lateral, and plantar surfaces of each foot to completely cover the treatment area.

- Once QUTENZA is applied, leave in place for 30 minutes on the feet (DPN).
- To ensure QUTENZA maintains contact with the treatment area, a dressing, such as rolled gauze, may be used. Remove the nitrile gloves after the application.
- Instruct the patient not to touch QUTENZA or the treatment area.

Remove

- Put on nitrile (not latex) gloves. Remove QUTENZA by gently and slowly rolling inward.

Cleanse

- After removal of QUTENZA, generously apply Cleansing Gel to the treatment area and leave on for at least one minute. Remove Cleansing Gel with a dry wipe and gently wash the area with mild soap and water. Dry thoroughly.

- Dispose of all treatment materials as described [see Dosage and Administration (2.1)] .
- Inform the patient that the treated area may be sensitive for a few days to heat (e.g., hot showers/baths, direct sunlight, vigorous exercise).

3 DOSAGE FORMS AND STRENGTHS

QUTENZA topical system contains 8% capsaicin (640 mcg per cm^2). Each topical system contains a total of 179 mg of capsaicin. Each topical system is 14 cm x 20 cm (280 cm^2) and consists of an adhesive side containing the active substance and an outer surface backing layer. The adhesive side is covered with a removable, clear, unprinted, diagonally cut, release liner. The outer surface of the backing layer is imprinted with “capsaicin 8%”.

4 CONTRAINDICATIONS

None.

5 WARNINGS AND PRECAUTIONS

5.1 Severe Irritation with Unintended Capsaicin Exposure

Unintended exposure to capsaicin can cause severe irritation of eyes, mucous membranes, respiratory tract, and skin in healthcare professionals, patients, and others. Ensure that the recommended procedures and protective measures are used when administering QUTENZA [see Dosage and Administration (2.1)].

Eye and Mucous Membrane Exposure

• For healthcare professionals:

○ Wear nitrile gloves when administering QUTENZA and avoid unnecessary contact with items in the room, including items that the patient may later have contact with, such as horizontal surfaces and bedsheets.

○ Use of a face mask and protective glasses is advisable.

• Do not apply QUTENZA to the patient’s face, eyes, mouth, nose, or scalp to avoid risk of exposure to eyes or mucous membranes.

• Accidental exposure to the eyes and mucous membranes can occur from touching QUTENZA or items exposed to capsaicin and then touching the eyes and mucous membranes.

• If irritation of eyes or mucous membranes occurs, flush eyes and mucous membranes with cool water. Remove the affected individual (healthcare professional or patient) from the vicinity of QUTENZA.

Respiratory Tract Exposure

- Aerosolization of capsaicin can occur upon rapid removal of QUTENZA. Therefore, remove QUTENZA gently and slowly by rolling the adhesive side inward [see Dosage and Administration (2.1, 2.3)] .
- Inhalation of airborne capsaicin can result in coughing or sneezing. Administer QUTENZA in a well-ventilated treatment area. Provide supportive medical care if shortness of breath develops. If irritation of airways occurs, remove the affected individual (healthcare professional or patient) from the vicinity of QUTENZA. If respiratory irritation worsens or does not resolve, do not re-expose the affected healthcare professional or patient to QUTENZA [see Adverse Reactions (6.2)].

Skin Exposure

- If skin not intended to be treated is exposed to QUTENZA, apply Cleansing Gel for one minute and wipe off with dry gauze. After the Cleansing Gel has been wiped off, wash the area with soap and water.

Thoroughly clean all areas that had contact with QUTENZA and properly dispose of QUTENZA, associated packaging, Cleansing Gel, gloves, and other treatment materials in accordance with local biomedical waste procedures [see Dosage and Administration (2.1, 2.3)] .

5.2 Application-Associated Pain

Even following use of a local anesthetic prior to administration of QUTENZA, patients may experience substantial procedural pain and burning upon application of QUTENZA and following removal of QUTENZA. Prepare to treat acute pain during and following the application procedure with local cooling and/or appropriate analgesic medication.

5.3 Increase in Blood Pressure

In clinical trials, transient increases in blood pressure occurred during or shortly after exposure to QUTENZA. The changes averaged less than 10 mm Hg, although some patients had greater increases and these changes lasted for approximately two hours after QUTENZA removal. Increases in blood pressure were unrelated to the pretreatment blood pressure but were related to treatment-related increases in pain. Monitor blood pressure periodically during and following the treatment procedure and provide adequate support for treatment-related pain.

Patients with unstable or poorly controlled hypertension, or a recent history of cardiovascular or cerebrovascular events, may be at an increased risk of adverse cardiovascular effects. Consider these factors prior to initiating QUTENZA treatment.

5.4 Sensory Function

Reductions in sensory function have been reported following administration of QUTENZA. Decreases in sensory functions are generally minor and temporary (including to thermal and other harmful stimuli). All patients with pre-existing sensory deficits should be clinically assessed for signs of sensory deterioration or loss prior to each application of QUTENZA. If sensory deterioration or loss is detected or pre-existing sensory deficit worsens, continued use of QUTENZA treatment should be reconsidered.

5.5 Severe Application Site Burns

Cases of full-thickness (third-degree) and deep partial-thickness (second-degree) burns have been reported following administration of QUTENZA. Cases of full-thickness (third-degree) burns, requiring hospitalization and skin grafting have been reported in patients who received QUTENZA for an unapproved indication and/or frequency of dosing at an application site where there had been prior skin trauma [see Adverse Reactions (6.2)]. Ensure that dosage and administration recommendations are followed [see Dosage and Administration (2)].

6 ADVERSE REACTIONS

The following serious adverse reactions are discussed elsewhere in the labeling:

- Severe Irritation Due to Accidental Exposure of Eyes, Skin, Respiratory Tract, and Mucous Membranes [see Warning and Precautions (5.1)]
- Application-Associated Pain [see Warnings and Precautions (5.2)]
- Increase in Blood Pressure [see Warnings and Precautions (5.3)]
- Sensory Function Reduction [see Warning and Precautions (5.4)]
- Severe Application Site Burns [see Warning and Precautions (5.5)]

6.1 Clinical Trials Experience

Because clinical trials are conducted under widely varying conditions, adverse reaction rates observed in the clinical trials of a drug cannot be directly compared to rates in the clinical trials of other drugs and may not reflect the rates observed in clinical practice.

Across all controlled and uncontrolled clinical trials, 2848 patients have received QUTENZA. A total of 924 patients received more than one treatment application and 732 patients were followed for 48 weeks or longer. A total of 590 DPN patients and 1112 PHN patients have received QUTENZA across all controlled and uncontrolled clinical trials.

Among patients treated with QUTENZA, 1% discontinued prematurely due to an adverse event.

Most Common Adverse Reactions in all Controlled Clinical Trials

In all controlled clinical trials, adverse reactions occurring in ≥5% of patients in the QUTENZA group and at an incidence at least 1% greater than in the control group were application site erythema, application site pain, and application site pruritus.

The majority of application site reactions were transient and self-limited. Transient increases in pain were commonly observed on the day of treatment in patients treated with QUTENZA. Pain increases occurring during QUTENZA application usually began to resolve after QUTENZA removal. On average, pain scores returned to baseline by the end of the treatment day and then remained at or below baseline levels. A majority of QUTENZA-treated patients in clinical trials had adverse reactions with a maximum intensity of "mild" or "moderate".

Postherpetic Neuralgia (PHN)

Table 1 summarizes all adverse reactions, regardless of causality, occurring in >1% of patients with PHN in the QUTENZA group for which the incidence was at least 1% greater than in the control group.

TABLE 1: Adverse Reaction Incidence (%) in Controlled Double-blind Trials in Postherpetic Neuralgia (Events in >1% of QUTENZA-treated Patients and at Least 1% Greater in the QUTENZA Group than in the Control Group)
Body System Preferred Term | QUTENZA 60 minutes (N=622) % | Control 60 minutes (N=495) %
General Disorders and Administration Site Conditions
Application site erythema | 63 | 54
Application site pain | 42 | 21
Application site pruritus | 6 | 4
Application site papules | 6 | 3
Application site edema | 4 | 1
Application site swelling | 2 | 1
Application site dryness | 2 | 1
Infections and Infestations
Nasopharyngitis | 4 | 2
Bronchitis | 2 | 1
Sinusitis | 3 | 1
Gastrointestinal Disorders
Nausea | 5 | 2
Vomiting | 3 | 1
Skin and Subcutaneous Tissue Disorder
Pruritus | 2 | < 1
Vascular Disorders
Hypertension | 2 | 1

Less common adverse reactions (<1%) with QUTENZA observed during PHN clinical trials included: palpitations, tachycardia, eye pruritus, application site reactions (such as urticaria, paresthesia, dermatitis, hyperesthesia).

Neuropathic Pain Associated with Diabetic Peripheral Neuropathy (DPN)

Table 2 summarizes all adverse reactions, regardless of causality, occurring in >1% of patients with DPN in the QUTENZA group for which the incidence was at least 1% greater than in the control group.

TABLE 2: Adverse Reaction Incidence (%) in Double-blind Controlled Trials in Neuropathic Pain Associated with Diabetic Peripheral Neuropathy (Events in >1% of QUTENZA-treated Patients and at Least 1% Greater in the QUTENZA Group than in the Control Group)
Body System; Preferred Term | QUTENZA; 30 minutes; (N=186); % | Control; 30 minutes; (N=183); %
General Disorders and Administration Site Conditions
Application site reactions
Burning sensation | 14 | 3
Application site pain | 10 | 2
Erythema | 2 | 0
Injury, Poisoning and Procedural Complications
Excoriation | 2 | 0
Musculoskeletal and Connective Tissue Disorders
Pain in extremity | 11 | 6
Nervous System Disorders
Headache | 3 | 2
Respiratory, Thoracic and Mediastinal Disorders
Upper respiratory symptoms
Upper respiratory tract infection | 4 | < 1
Cough | 2 | < 1
Vascular Disorders
Hypertension | 2 | < 1

Less common adverse reactions (<1%) with QUTENZA observed during DPN clinical trials included: dizziness, dysesthesia, blister.

6.2 Postmarketing Experience

Because adverse reactions are reported voluntarily from a population of uncertain size, it is not always possible to reliably estimate their frequency or establish a causal relationship to drug exposure.

The following adverse reactions have been identified during post approval use of QUTENZA: deep partial-thickness (second-degree) and full-thickness (third-degree) burns and scarring; accidental exposure (including eye pain, cough, eye and throat irritation) [see Warnings and Precautions (5.1, 5.5)].

7 DRUG INTERACTIONS

No clinical drug interaction studies have been performed.

Data from in vitro cytochrome P450 inhibition and induction studies show that capsaicin does not inhibit or induce liver cytochrome P450 enzymes at concentrations which far exceed those measured in blood samples. Therefore, interactions with systemic medicinal products are unlikely.

8 USE IN SPECIFIC POPULATIONS

8.1 Pregnancy

Risk Summary

Capsaicin is negligibly absorbed systemically following topical administration of QUTENZA, and maternal use is not expected to result in the fetal exposure to QUTENZA. In animal reproductive studies, no evidence of malformations were observed when capsaicin was administered daily by the topical route to pregnant rats and rabbits during the period of organogenesis at doses of up to 11- and 37-times, respectively, the maximum recommended human dose (MRHD) of QUTENZA at 716 mg capsaicin per day (4 topical systems containing 179 mg/topical system). In a peri- and postnatal development study, no adverse effects were observed when capsaicin was administered daily by the topical route to rats during implantation to weaning at doses of up to 11-times the MRHD (see Data).

The estimated background risk of major birth defects and miscarriage for the indicated population is unknown. All pregnancies have a background risk of birth defect, loss, or other adverse outcomes. In the U.S. general population, the estimated background risk of major birth defects and miscarriage in clinically recognized pregnancies is 2% to 4% and 15% to 20%, respectively.

Data
Animal Data

There was no evidence of fetal malformations in embryofetal developmental toxicological studies conducted in pregnant rats and rabbits in which QUTENZA (rats) or capsaicin liquid (rabbits) were applied once daily for a 3-hour duration during the period of fetal organogenesis at doses up to 11-times (rat, 32 mg QUTENZA /day) and 37-times (rabbit, 260 mg capsaicin/day) the MRHD based on a C max exposure comparison.

In a peri- and postnatal reproduction toxicology study, pregnant female rats were treated with QUTENZA at doses up to 32 mg QUTENZA/rat/day applied once daily for a 3-hour duration during gestation and lactation (from Gestation Day 7 through Lactation Day 20). Analyses of milk samples on Day 14 of the lactation period demonstrated measurable levels of capsaicin in the dam's milk at all dose levels. There were no effects on survival, growth, learning and memory tests (passive avoidance and water maze), sexual maturation, mating, pregnancy, and fetal development in the offspring of mothers treated with capsaicin up to 32 mg QUTENZA /rat/day (11-times the MRHD based on C max exposure).

8.2 Lactation

Risk Summary
Capsaicin is negligibly absorbed systemically by the mother following topical administration of QUTENZA, and breastfeeding is not expected to result in exposure of the infant to QUTENZA [see Clinical Pharmacology (12.3)] . There are no data on the effects of capsaicin on milk production. To minimize potential direct exposure of QUTENZA to the breastfed infant, avoid applying QUTENZA directly to the nipple and areola.

The developmental and health benefits of breastfeeding should be considered along with the mother’s clinical need for QUTENZA and any potential adverse effects on the breastfed infant from QUTENZA or from the underlying maternal condition.

8.3 Females and Males of Reproductive Potential

Infertility
In a fertility and reproductive toxicology study, administration of QUTENZA at 13-times the MRHD to male rats for 3 hours/day for 49 days resulted in a statistically significant reduction in the number and percent of motile sperm; however, these reductions did not adversely affect fertility [see Nonclinical Toxicology (13.1)] . As this animal model has a large excess of sperm-generating capacity relative to the threshold necessary for fertilization, the lack of an effect on fertility in this species is of unknown clinical significance for males of reproductive potential treated with the MRHD.

8.4 Pediatric Use

The safety and effectiveness of QUTENZA in patients younger than 18 years of age have not been studied.

8.5 Geriatric Use

In controlled clinical trials of QUTENZA in neuropathic pain associated with postherpetic neuralgia, 75% of patients were 65 years and older and 43% of patients were 75 years and older. The safety and effectiveness were similar in geriatric patients and younger patients. No dose adjustments are required in geriatric patients.

10 OVERDOSAGE

There is no clinical experience with QUTENZA overdose in humans.

There is no specific antidote for overdose with capsaicin. In case of suspected overdose, remove QUTENZA gently, apply Cleansing Gel for one minute, wipe off with dry gauze, and gently wash the area with soap and water. Use supportive measures and treat symptoms as clinically warranted.

11 DESCRIPTION

QUTENZA (capsaicin) 8% topical system contains capsaicin in a localized dermal delivery system. The capsaicin in QUTENZA is a synthetic equivalent of the naturally occurring compound found in chili peppers. Capsaicin is soluble in alcohol, acetone, and ethyl acetate and very slightly soluble in water.

QUTENZA is a single-use topical system stored in a foil pouch. Each QUTENZA is 14 cm x 20 cm (280 cm^2) and consists of a polyester backing film coated with a drug-containing silicone adhesive mixture and covered with a removable polyester release liner.

The backing film is imprinted with “capsaicin 8%”. Each QUTENZA contains a total of 179 mg of capsaicin (8% in adhesive, 80 mg per gram of adhesive) or 640 micrograms (mcg) of capsaicin per square cm of topical system.

The empirical formula is C18H27NO3, with a molecular weight of 305.42. The chemical compound capsaicin [(E)-8-methyl-N-vanillyl-6-nonenamide] is an activating ligand for transient receptor potential vanilloid 1 receptor (TRPV1) and it has the following structure:

FIGURE 1: Structural Formula of Capsaicin

QUTENZA contains the following inactive ingredients: diethylene glycol monoethyl ether, dimethicone, ethyl cellulose, polyester film, silicone adhesive, and white ink.

QUTENZA is supplied with a Cleansing Gel which is used to remove residual capsaicin from the skin after treatment. Cleansing Gel consists of the following ingredients: butylated hydroxyanisole, carbomer copolymer, edetate disodium, polyethylene glycol, purified water, and sodium hydroxide.

12 CLINICAL PHARMACOLOGY

12.1 Mechanism of Action

Capsaicin is an agonist for the transient receptor potential vanilloid 1 receptor (TRPV1), which is an ion channel-receptor complex expressed on nociceptive nerve fibers in the skin. Topical administration of capsaicin causes an initial enhanced stimulation of the TRPV1-expressing cutaneous nociceptors that may be associated with painful sensations. This is followed by pain relief thought to be mediated by a reduction in TRPV1-expressing nociceptive nerve endings [see Clinical Pharmacology (12.2)] . Over the course of several months, there may be a gradual re-emergence of painful neuropathy thought to be due to TRPV1 nerve fiber reinnervation of the treated area.

12.2 Pharmacodynamics

Two studies evaluated the pharmacodynamic effects of QUTENZA on sensory function and epidermal nerve fiber (ENF) density in healthy volunteers. Consistent with the known pharmacodynamic effects of capsaicin on TRPV1-expressing nociceptive nerve endings, reduced ENF density and minor changes in cutaneous nociceptive function (heat detection and sharp sensation) were noted one week after exposure to QUTENZA. ENF density reduction and sensory changes were fully reversible.

12.3 Pharmacokinetics

Pharmacokinetic data in humans showed transient, low (<5 ng/mL) systemic exposure to capsaicin in about one-third of PHN patients following 60-minute applications of QUTENZA. The highest plasma concentration of capsaicin detected was 4.6 ng/mL and occurred immediately after QUTENZA removal. Most quantifiable levels were observed at the time of QUTENZA removal and were below the limit of quantitation 3 to 6 hours after QUTENZA removal. No detectable levels of metabolites were observed in any subject.

13 NONCLINICAL TOXICOLOGY

13.1 Carcinogenesis, Mutagenesis, Impairment of Fertility

Carcinogenesis

Adequate carcinogenicity studies have not been conducted with QUTENZA or capsaicin.

Mutagenesis

Capsaicin was not mutagenic in the Ames, mouse micronucleus, and chromosomal aberration in human peripheral blood lymphocytes assays. As with other catechol-containing compounds (e.g., dopamine), capsaicin showed a weak mutagenic response in the mouse lymphoma assay.

Impairment of Fertility

A fertility and reproductive toxicology study was conducted in rats with exposure to QUTENZA daily for 3 hours/day beginning 28 days before cohabitation, through cohabitation, and continuing through the day before sacrifice (approximately 49 days of treatment). The results revealed a statistically significant reduction in the number and percent of motile sperm. Sperm motility obtained from the vas deferens was reduced in all capsaicin treatment groups (16, 24 and 32 mg QUTENZA/rat/day). Though a “no effect” level was not determined, dose levels used in the study correspond to a 13- to 28-fold exposure margin over the mean C max associated with the MRHD. Sperm counts were reduced in the vas deferens or cauda epididymis in the 24 and 32 mg QUTENZA/rat/day dose groups (79% and 69%, respectively) compared to the placebo topical system-treated control group; however, these reductions did not adversely affect fertility. As this animal model has a large excess of sperm-generating capacity relative to the threshold necessary for fertilization, the lack of an effect on fertility in this species is of unknown significance for human risk assessment.

14 CLINICAL STUDIES

14.1 Postherpetic Neuralgia

The efficacy of QUTENZA was established in two 12-week, double-blind, randomized, dose-controlled, multicenter clinical trials. These studies enrolled patients with postherpetic neuralgia (PHN) persisting for at least 6 months following healing of herpes zoster rash and a baseline score of 3-9 on an 11-point Numerical Pain Rating Scale (NPRS) ranging from 0 (no pain) to 10 (worst possible pain). QUTENZA and a control topical system were each applied as a single, 60-minute application. The control used in these studies looked similar to QUTENZA but contained a low concentration of the active ingredient, capsaicin (3.2 mcg/cm^2, 0.04% w/w), to retain blinding regarding the known application site reactions of capsaicin (such as burning and erythema). The baseline mean pain score across the 2 studies was approximately 6.0. Patients who entered the study on stable doses of pain-control medications were required to keep dosing stable throughout the duration of the study. Approximately half of the patients were taking concomitant medications, including anticonvulsants, non-SSRI antidepressants, or opioids for their PHN at study entry. Prior to application, a topical anesthetic was applied to the treatment area for 60 minutes. Patients were permitted to use local cooling and additional analgesic medications for treatment-related discomfort as needed through Day 5. Patients recorded their pain daily in a diary.

PHN Study 1: In this 12-week study, the QUTENZA group demonstrated a greater reduction in pain compared to the control group during the primary assessment at Week 8. The percent change in average pain from baseline to Week 8 was -18% (±2%) for the low-dose control and -29% (±2%) for QUTENZA.

For various degrees of improvement in pain from baseline to study endpoint, Figure 2 shows the fraction of patients achieving that degree of improvement. The figure is cumulative, so that patients whose change from baseline is, for example, 50%, are also included at every level of improvement below 50%. Patients who did not complete the study through Week 12 or who showed no improvement at Week 12 were assigned 0% improvement. Some patients experienced a decrease in pain as early as Week 1, which persisted throughout the study. The proportion of patients experiencing ≥30% reduction in pain intensity from baseline for each week through Week 12 is shown in Figure 3.

FIGURE 2: Patients Achieving Various Percentages of Reduction in Pain Intensity at Week 12 – Study 1

FIGURE 3: Weekly Proportion of Patients Achieving ≥30% Pain Intensity Reduction – Study 1*

PHN Study 2: In this 12-week study, the QUTENZA group demonstrated a greater reduction in pain compared to the control group during the primary assessment at Week 8. The percent change in average pain from baseline to Week 8 was -26% (±2%) for the low-dose control and -33% (±2%) for QUTENZA.

For various degrees of improvement in pain from baseline to study endpoint, Figure 4 shows the fraction of patients achieving that degree of improvement. The figure is cumulative, so that patients whose change from baseline is, for example, 50%, are also included at every level of improvement below 50%. Patients who did not complete the study through Week 12 or who showed no improvement at Week 12 were assigned 0% improvement. Some patients experienced a decrease in pain as early as Week 1, which persisted throughout the study. The proportion of patients achieving ≥30% reduction in pain intensity from baseline for each week through Week 12 is shown in Figure 5.

FIGURE 4: Patients Achieving Various Percentages of Reduction in Pain Intensity at Week 12 – Study 2

FIGURE 5: Weekly Proportion of Patients Achieving ≥ 30% Pain Intensity Reduction – Study 2*

14.2 Neuropathic Pain Associated with Diabetic Peripheral Neuropathy

The efficacy of QUTENZA was established in one 12-week, double-blind, randomized, placebo-controlled, multicenter study. This study enrolled patients with neuropathic pain associated with diabetic peripheral neuropathy (DPN) diagnosed at least 1 year prior to screening and an average pain score of ≥ 4 over the baseline period on an 11-point Numerical Pain Rating Scale (NPRS) ranging from 0 (no pain) to 10 (worst possible pain). QUTENZA and placebo were each applied as a single, 30-minute application. The placebo used in this study was similar to QUTENZA but did not contain an active ingredient. The baseline mean pain score in this study was 6.51 (SD 1.45) and was similar in both groups. Patients who entered the study on stable doses of pain-control medications were required to keep dosing stable throughout the duration of the study. Use of opioid medication other than short-acting rescue medication was not allowed during the study. Concomitant medications for neuropathic pain associated with DPN were taken during the study by 47.2% of the patients and included anticonvulsants and non-SSRI antidepressants. Prior to application, a topical anesthetic was applied to the treatment area for 60 minutes. Patients were permitted to use local cooling and additional analgesic medications for treatment-related discomfort as needed through Day 5. Patients recorded their pain daily.

In this 12-week study, the percent change in average pain from baseline to Week 12 was higher in the QUTENZA group compared to the placebo group. The percent change in average pain from baseline to Week 12 was -22% (±3%) for placebo and -30% (±3%) for QUTENZA. The least-squares mean change was -1.92 on the 11-point NPRS scale for QUTENZA, vs -1.37 for placebo, a least-squares mean difference of -0.56 (95% CI -0.98, -0.14).

For various degrees of improvement in pain from baseline to study endpoint, Figure 6 shows the fraction of patients achieving that degree of improvement. The figure is cumulative, so that patients whose change from baseline is, for example, 50%, are also included at every level of improvement below 50%. Patients who did not complete the study through Week 12 or who showed no improvement at Week 12 were assigned 0% improvement. The proportion of patients experiencing ≥30% reduction in pain intensity from baseline for each week through Week 12 is shown in Figure 7.

FIGURE 6: Patients Achieving Various Percentages of Reduction in Pain Intensity at Week 12

FIGURE 7: Weekly Proportion of Patients Achieving ≥30% Pain Intensity Reduction*

16 HOW SUPPLIED/STORAGE AND HANDLING

16.1 How Supplied

QUTENZA (capsaicin) 8% topical system is a single-use topical system stored in a sealed pouch (NDC 72512-920-00).

QUTENZA is 14 cm x 20 cm (280 cm^2) and consists of an adhesive side containing the active substance and an outer surface backing layer. The adhesive side is covered with a removable, clear, unprinted, diagonally cut, release liner. The outer surface of the backing layer is imprinted with “capsaicin 8%”.

Cleansing Gel is provided in a 50 g tube.

QUTENZA is available in the following presentations:

Carton of one topical system and one 50 g tube of Cleansing Gel (NDC 72512-928-01).

Carton of two topical systems and one 50 g tube of Cleansing Gel (NDC 72512-929-01).

Carton of four topical systems and three 50 g tubes of Cleansing Gel (NDC 72512-930-01).

16.2 Storage

Store carton between 20°C to 25°C (68°F to 77°F). Excursions between 15°C and 30°C (59°F and 86°F) are allowed.

Keep QUTENZA in the sealed pouch until immediately before use.

16.3 Handling and Disposal

Unintended exposure to capsaicin can cause severe irritation of eyes, skin, respiratory tract, and mucous membranes. Wear nitrile (not latex) gloves while administering QUTENZA. Use of a face mask and protective glasses is advisable. Immediately after use, dispose of used and unused QUTENZA, QUTENZA clippings, associated packaging, Cleansing Gel, and all other potentially contaminated treatment supplies in accordance with local biomedical waste procedures [see Dosage and Administration (2), Warnings and Precautions (5.1)] .

17 PATIENT COUNSELING INFORMATION

- Inform patients that accidental exposure to capsaicin from touching QUTENZA or items exposed to capsaicin can cause severe irritation of eyes, mucous membranes, respiratory tract, and skin.
- Instruct patients not to touch their eyes and other unintended target area and that if irritation of eyes or airways occurs, or if any of the side effects become severe, to notify their doctor immediately.
- Inform patients that acute pain during and after the QUTENZA application procedure may be treated with local cooling or analgesic medication, as appropriate. Inform patients of the potential risk for frostbite with excessive use of cooling. It is recommended to use cooling packs from the refrigerator (not from the freezer) and to avoid direct application to the skin.
- Advise patients to seek medical attention if they experience persistent severe pain or skin lesions such as blisters after the QUTENZA application procedure.
- Inform patients that, as a result of treatment-related increases in pain, small transient increases in blood pressure may occur during and shortly after QUTENZA treatment and that blood pressure will be monitored during the treatment procedure. Instruct patients to inform the physician if they have experienced any recent cardiovascular events.
- Inform patients that the treated area may be sensitive to heat (e.g., hot showers/bath, direct sunlight, vigorous exercise) for a few days following treatment.

Manufactured for Averitas Pharma, Inc., Morristown, NJ 07960, USA

by Lohmann Therapie-Systeme AG (LTS), Andernach, Germany

QUTENZA® is a registered trademark of Averitas Pharma, Inc.

PRINCIPAL DISPLAY PANEL - Carton Label (1 Topical System)

NDC 72512-928-01

1

One single-use topical system (179 mg capsaicin)
One single-use 50 g tube of Cleansing Gel

Qutenza ®
(capsaicin) 8% topical system

Rx only. For topical use only.

Dosage/Instructions for Use: See Full Prescribing Information.

QUTENZA contains capsaicin and may cause irritation.

Do not dispense to patients for self-administration or handling.

QUTENZA should be administered by a physician or healthcare professional.

Only a healthcare professional should open the QUTENZA carton or pouch.

Use of nitrile gloves is required when handling QUTENZA. Do not use latex gloves.

Averitas A Grunenthal Company
Manufactured for Averitas Pharma, Inc, Morristown, NJ 07960, USA by Lohmann Therapie-Systeme AG (LTS) Andernach, Germany © Averitas Pharma, Inc. 2023
For questions about QUTENZA call 1-877-900-6479 Rev. February 2023

Store carton between 20°C and 25°C (68°F and 77°F).
Excursions between 15°C and 30°C (59°F and 86°F) are allowed.
Keep QUTENZA in the sealed pouch until immediately before use.
Store out of the reach of children and pets.

Inactive Ingredients:
QUTENZA: diethylene glycol monoethyl ether, dimethicone, ethyl cellulose, polyester film, silicone adhesive, and white ink

Cleansing Gel: butylated hydroxyanisole, carbomer copolymer, edetate disodium, polyethylene glycol, purified water, and sodium hydroxide

PRINCIPAL DISPLAY PANEL - Carton Label (2 Topical Systems)

NDC 72512-929-01

2

Two single-use topical systems (179 mg capsaicin)
One single-use 50 g tube of Cleansing Gel

Qutenza ®
(capsaicin) 8% topical system

Rx only. For topical use only.

Dosage/Instructions for Use: See Full Prescribing Information.

QUTENZA contains capsaicin and may cause irritation.

Do not dispense to patients for self-administration or handling.

QUTENZA should be administered by a physician or healthcare professional.

Only a healthcare professional should open the QUTENZA carton or pouch.

Use of nitrile gloves is required when handling QUTENZA. Do not use latex gloves.

Averitas A Grunenthal Company
Manufactured for Averitas Pharma, Inc, Morristown, NJ 07960, USA by Lohmann Therapie-Systeme AG (LTS) Andernach, Germany © Averitas Pharma, Inc. 2023
For questions about QUTENZA call 1-877-900-6479 Rev. February 2023

Store carton between 20°C and 25°C (68°F and 77°F).
Excursions between 15°C and 30°C (59°F and 86°F) are allowed.
Keep QUTENZA in the sealed pouch until immediately before use.
Store out of the reach of children and pets.

Inactive Ingredients:
QUTENZA: diethylene glycol monoethyl ether, dimethicone, ethyl cellulose, polyester film, silicone adhesive, and white ink

Cleansing Gel: butylated hydroxyanisole, carbomer copolymer, edetate disodium, polyethylene glycol, purified water, and sodium hydroxide

PRINCIPAL DISPLAY PANEL - Carton Label (4 Topical Systems)

NDC 72512-930-01

4

Four-use topical systems (179 mg capsaicin)

Three single-use 50 g tube of Cleansing Gel

Qutenza ®
(capsaicin) 8% topical system

Rx only. For topical use only.

Dosage/Instructions for Use: See Full Prescribing Information.

QUTENZA contains capsaicin and may cause irritation.

Do not dispense to patients for self-administration or handling.

QUTENZA should be administered by a physician or healthcare professional.

Only a healthcare professional should open the QUTENZA carton or pouch.

Use of nitrile gloves is required when handling QUTENZA. Do not use latex gloves.

Averitas A Grunenthal Company
Manufactured for Averitas Pharma, Inc, Morristown, NJ 07960, USA by Lohmann Therapie-Systeme AG (LTS) Andernach, Germany © Averitas Pharma, Inc. 2023
For questions about QUTENZA call 1-877-900-6479 Rev. February 2023

Store carton between 20°C and 25°C (68°F and 77°F).
Excursions between 15°C and 30°C (59°F and 86°F) are allowed.
Keep QUTENZA in the sealed pouch until immediately before use.
Store out of the reach of children and pets.

Inactive Ingredients:
QUTENZA: diethylene glycol monoethyl ether, dimethicone, ethyl cellulose, polyester film, silicone adhesive, and white ink

Cleansing Gel: butylated hydroxyanisole, carbomer copolymer, edetate disodium, polyethylene glycol, purified water, and sodium hydroxide